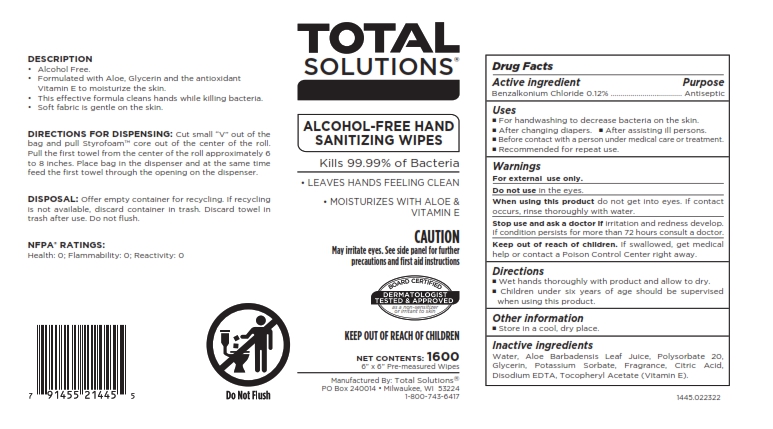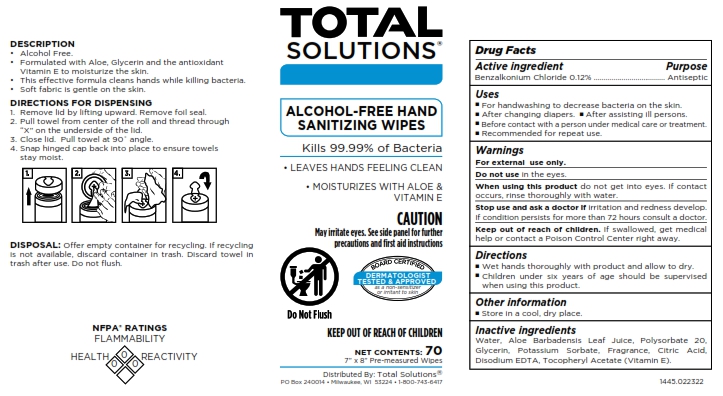 DRUG LABEL: Total Solutions Alcohol-Free Hand Sanitizing Wipes
NDC: 62819-445 | Form: CLOTH
Manufacturer: Athea Laboratories, Inc.
Category: otc | Type: HUMAN OTC DRUG LABEL
Date: 20250101

ACTIVE INGREDIENTS: BENZALKONIUM CHLORIDE 0.12 g/100 g
INACTIVE INGREDIENTS: WATER; CITRIC ACID; GLYCERIN; POLYSORBATE 20; ALOE BARBADENSIS LEAF; EDETATE DISODIUM; POTASSIUM SORBATE; ALPHA-TOCOPHEROL ACETATE

1445-Total Solutions Alcohol Free Hand Sanitizing Wipes

ACTIVE INGREDIENT

Benzalkonium Chloride 0.12%

PURPOSE

Antiseptic

INDICATIONS AND USAGE

- For handwashing to decrease bacteria on the skin.
- After changing diapers.
- After assisting ill persons.
- Before contact with a person under medical care or treatment.
- Recommended for repeat use.

WARNINGS

For external use only.

Do not use in the eyes.

When using this product do not get into eyes. If contact occurs, rinse thoroughly with water.

Stop use and ask a doctor if irritation and redness develop. If condition persists for more than 72 hours consult a doctor.

Keep out of reach of children. If swallowed, get medical help or contact a Poison Control Center right away.

DOSAGE AND ADMINISTRATION

- Wet hands thoroughly with product and allow to dry.
- Children under six years of age should be supervised when using this product.

OTHER SAFETY INFORMATION

- Store in a cool, dry place.

INACTIVE INGREDIENT

Water, Aloe Barbadensis Leaf Juice, Polysorbate 20, Glycerin, Potassium Sorbate, Fragrance, Citric Acid, Disodium EDTA, Tocopheryl Acetate (Vitamin E).